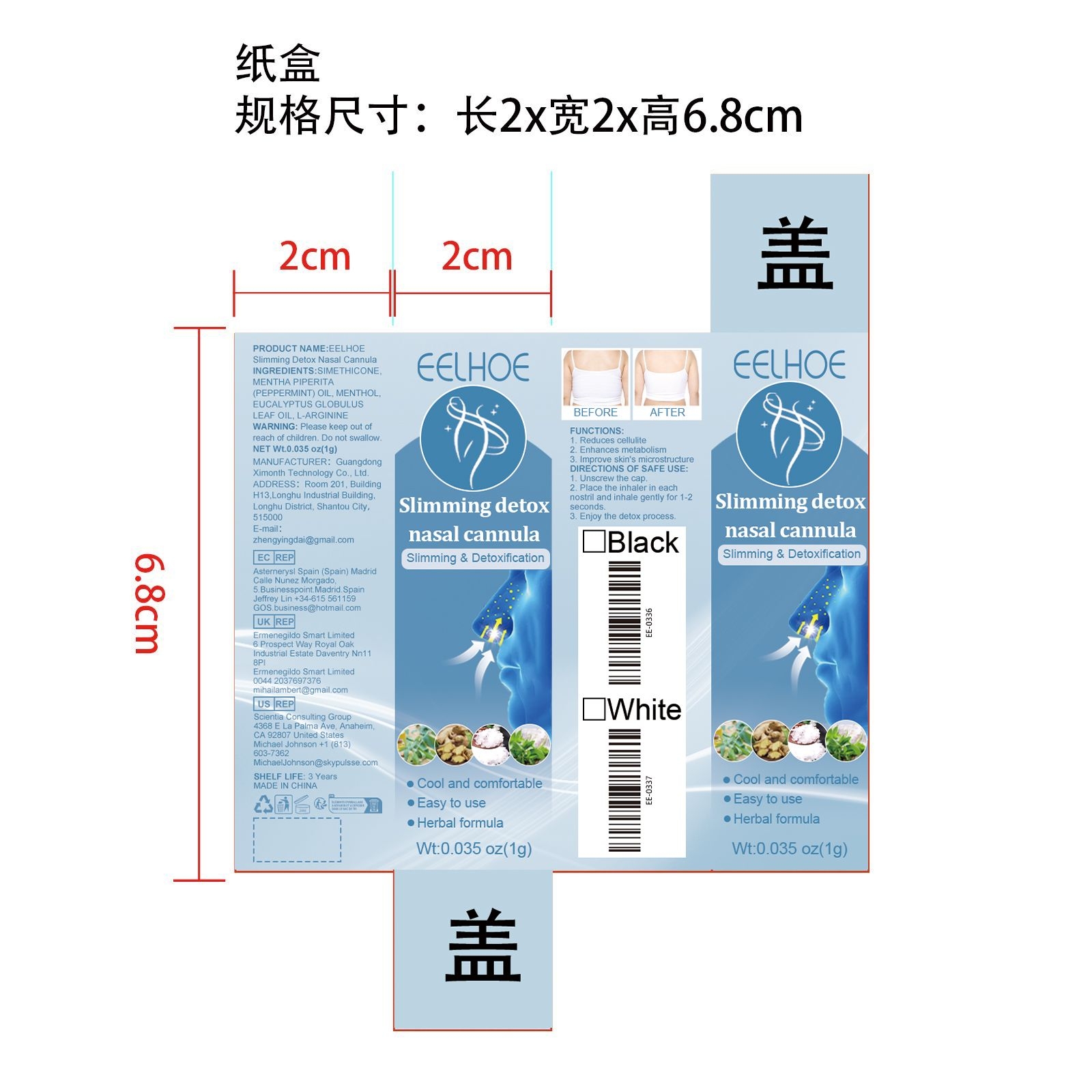 DRUG LABEL: Slimming Detox Nasal Cannula
NDC: 84660-012 | Form: CREAM
Manufacturer: Guangdong Ximonth Technology Co., Ltd.
Category: otc | Type: HUMAN OTC DRUG LABEL
Date: 20240909

ACTIVE INGREDIENTS: EUCALYPTUS OIL 0.15 g/1 g; MENTHOL, UNSPECIFIED FORM 0.2 g/1 g; ARGININE 0.1 g/1 g
INACTIVE INGREDIENTS: SILICON DIOXIDE 0.3 g/1 g; PEPPERMINT OIL 0.25 g/1 g

Active Ingredient(s)

MENTHA PIPERITA(PEPPERMINT) OIL、MENTHOL、EUCALYPTUS GLOBULUS LEAF OIL、L-ARGININE

Purpose

1. Reduces cellulite.
2. Enhances metabolism.
3. Improve skin's microstructure

Use

1. Unscrew the cap. 2. Place the inhaler in each nostril and inhale gently for 1-2 seconds. 3. Enjoy the detox process.

Warnings

Please keep out of reach of children.Do not swallow.Please clean your hands before use to ensure the best results from the product.Discontinue use if signs of irritation or rash occur.Store in a cool and dry place.

Do not use

Discontinue use if signs of irritation or rash occur.

STOP USE

Discontinue use if signs of irritation or rash occur.

KEEP OUT OF REACH OF CHILDREN

Please keep out of reach of children. Do not swallow.

STORAGE AND HANDLING

Avoid freezing and excessive heat above 40C (104F) ）

Store in a cool and dry place.

INACTIVE INGREDIENT

SIMETHICONE